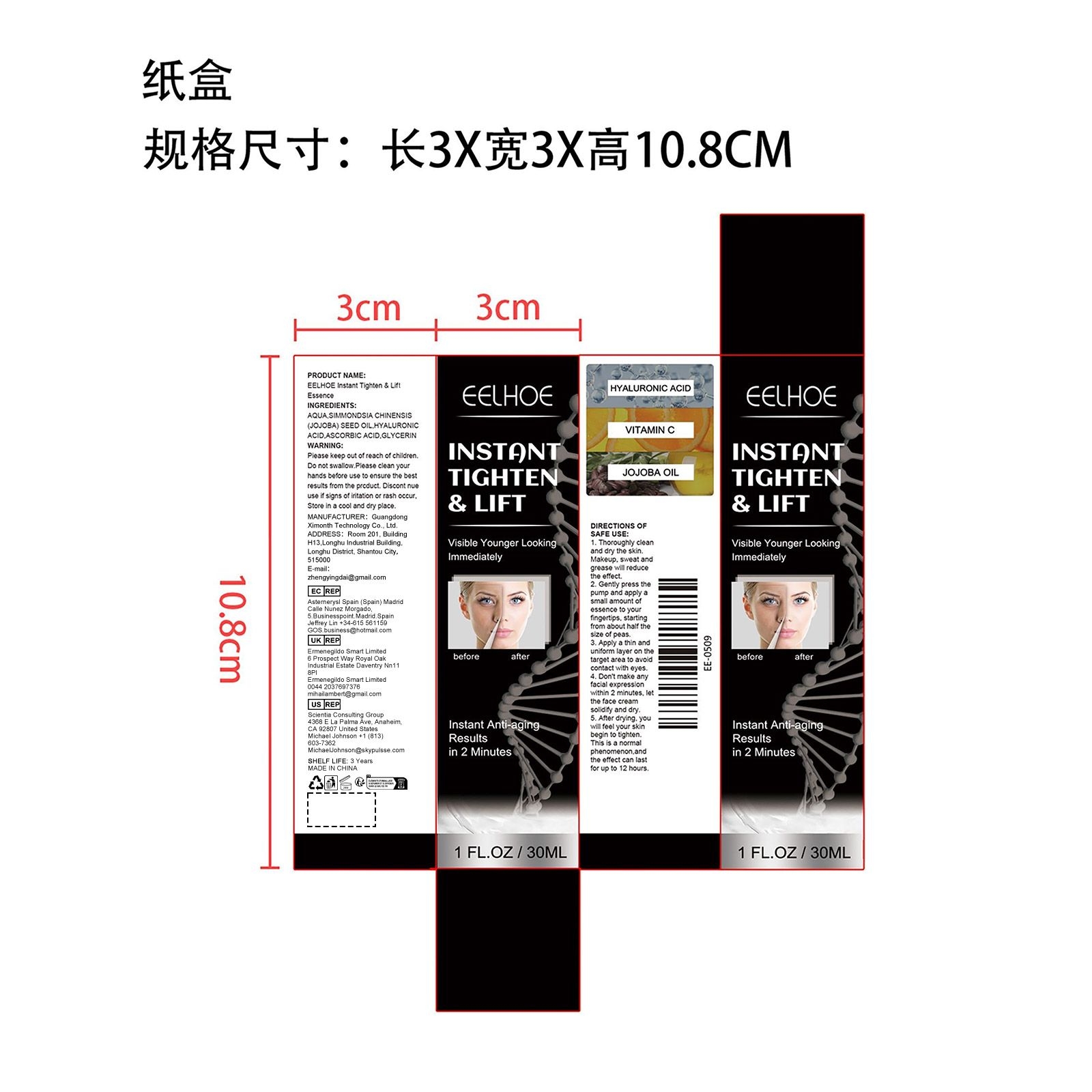 DRUG LABEL: Instant Tighten Lift Essence
NDC: 84660-018 | Form: LIQUID
Manufacturer: Guangdong Ximonth Technology Co., Ltd.
Category: otc | Type: HUMAN OTC DRUG LABEL
Date: 20240921

ACTIVE INGREDIENTS: HYALURONIC ACID 6 mg/30 mg; JOJOBA OIL 3 mg/30 mg; ASCORBIC ACID 4.5 mg/30 mg
INACTIVE INGREDIENTS: WATER 9 mL/30 mg; GLYCERIN 7.5 mg/30 mg

Active Ingredient(s)

SIMMONDSIA CHINENSIS(JOJOBA) SEED OIL、HYALURONIC ACID、ASCORBIC ACID

Purpose

Visible Younger Looking Immediately

Warnings

Please keep out of reach of children.Do not swallow.Please clean your hands before use to ensure the best results from the product.Discontinue use if signs of irritation or rash occur.Store in a cool and dry place.

Use

1. Thoroughly clean and dry the skin.Makeup, sweat and grease will reduce the effect. 2. Gently press the pump and apply a small amount of essence to your fingertips, starting from about half the size of peas. 3. Apply a thin and uniform layer on the target area to avoid contact with eyes. 4. Don't make any facial expression within 2 minutes, let the face cream solidify and dry. 5. After drying, you will feel your skin begin to tighten. This is a normal phenomenon,and the effect can last for up to 12 hours.

Do not use

Discontinue use if signs of irritation or rash occur.

STOP USE

Discontinue use if signs of irritation or rash occur.

KEEP OUT OF REACH OF CHILDREN

Please keep out of reach of children. Do not swallow.

STORAGE AND HANDLING

Avoid freezing and excessive heat above 40C (104F) ）

Store in a cool and dry place.

INACTIVE INGREDIENT

AQUA、GLYCERIN